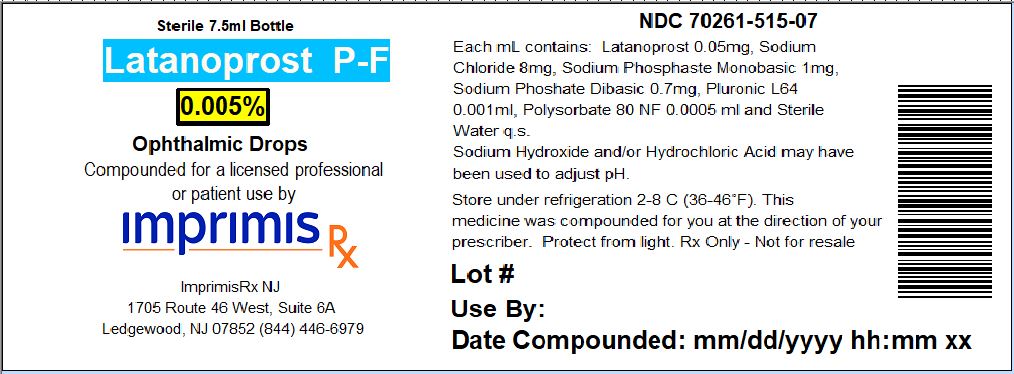 DRUG LABEL: Latanoprost PF
NDC: 70261-515 | Form: SOLUTION/ DROPS
Manufacturer: ImprimisRx NJ
Category: prescription | Type: HUMAN PRESCRIPTION DRUG LABEL
Date: 20180508

ACTIVE INGREDIENTS: LATANOPROST 0.05 mg/1 mL

STORAGE AND HANDLING

Store under refrigeration 2° to 8° C (36° to 46° F)